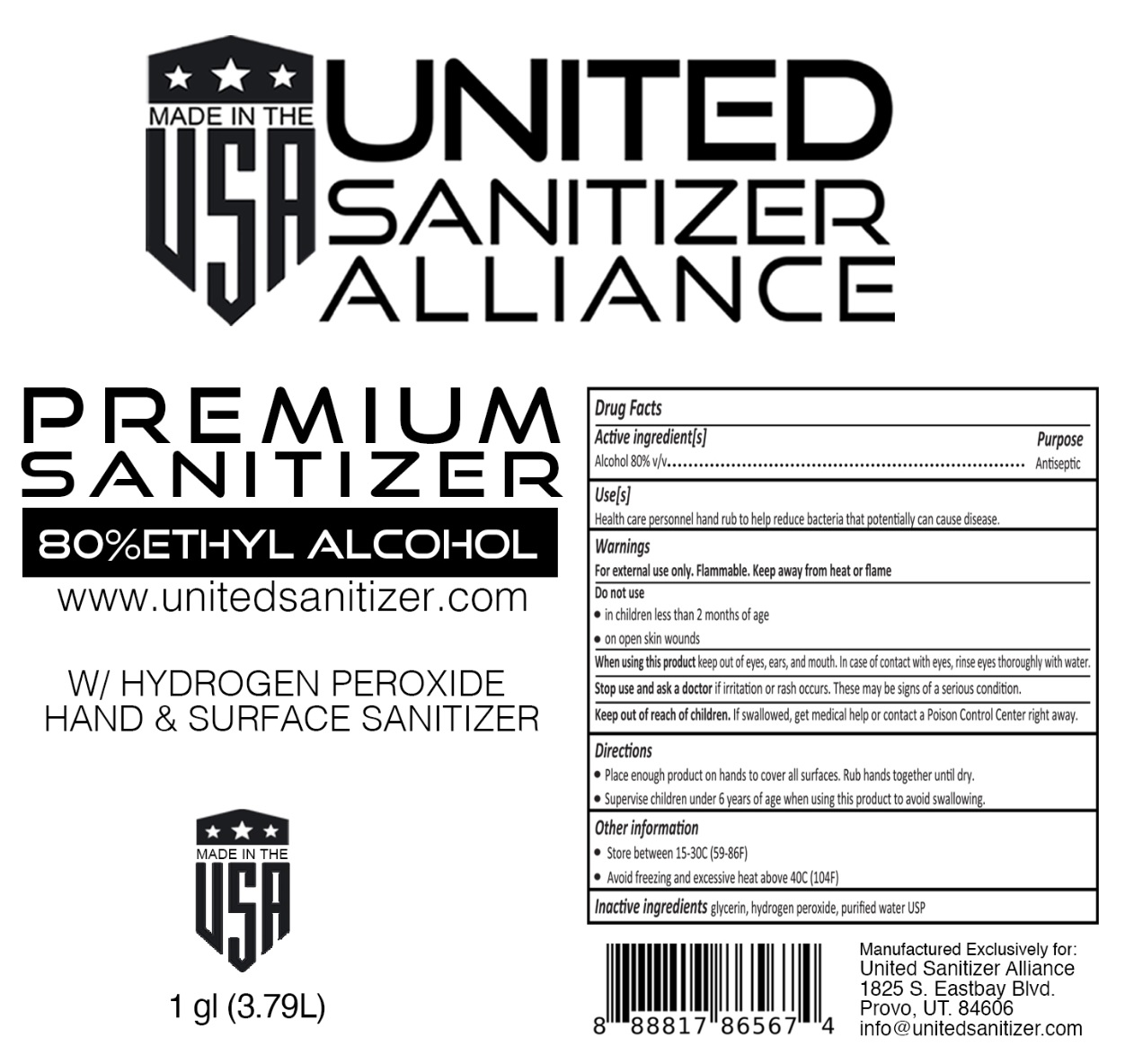 DRUG LABEL: UNITED SANITIZER ALLIANCE PREMIUM SANITIZER
NDC: 78608-512 | Form: LIQUID
Manufacturer: STAR VALLEY RESEARCH, LLC DBA United Sanitizer
Category: otc | Type: HUMAN OTC DRUG LABEL
Date: 20200603

ACTIVE INGREDIENTS: ALCOHOL 80 L/100 L
INACTIVE INGREDIENTS: GLYCERIN; HYDROGEN PEROXIDE; WATER

UNITED SANITIZER ALLIANCE PREMIUM SANITIZER

Active ingredient[s]

Alcohol 80% v/v

Purpose

Antiseptic

Use[s]

Health care personnel hand rub to help reduce bacteria that potentially can cause disease.

Warnings

For external use only. Flammable. Keep away from heat or flame.

Do not use

- in children less than 2 months of age
- on open skin wounds

When using this product keep out of eyes, ears, and mouth. In case of contact with eyes, rinse eyes thoroughly with water.

Stop use and ask a doctor if irritation or rash occurs. These may be signs of a serious condition.

Keep out of reach of children. If swallowed, get medical help or contact a Poison Control Center right away.

Directions

- Place enough product on hands to cover all surfaces. Rub hands together until dry.
- Supervise children under 6 years of age when using product to avoid swallowing.

Other information

- Store between 15-30C (59-86F)
- Avoid freezing and excessive heat above 40C (104F)

Inactive ingredients glycerin, hydrogen peroxide, purified water USP

80% ETHYL ALCOHOL

www.unitedsanitizer.com

W/ HYDROGEN PEROXIDE
HAND & SURFACE SANITIZER

MADE IN THE USA

Manufactured Exclusively for:
United Sanitizer Alliance
1825 S. Eastbay Blvd.
Provo, UT. 84606
info@unitedsanitizer.com